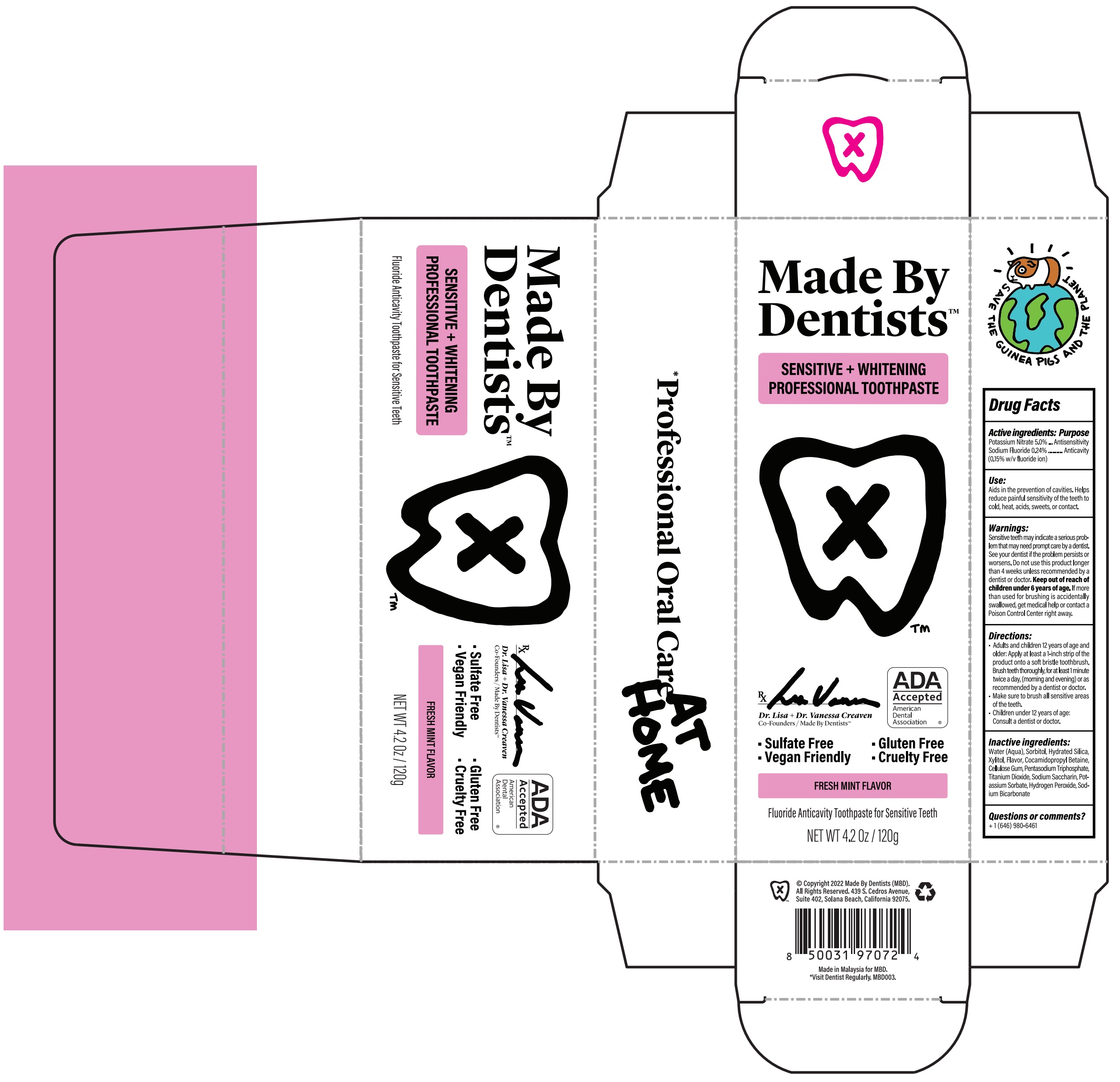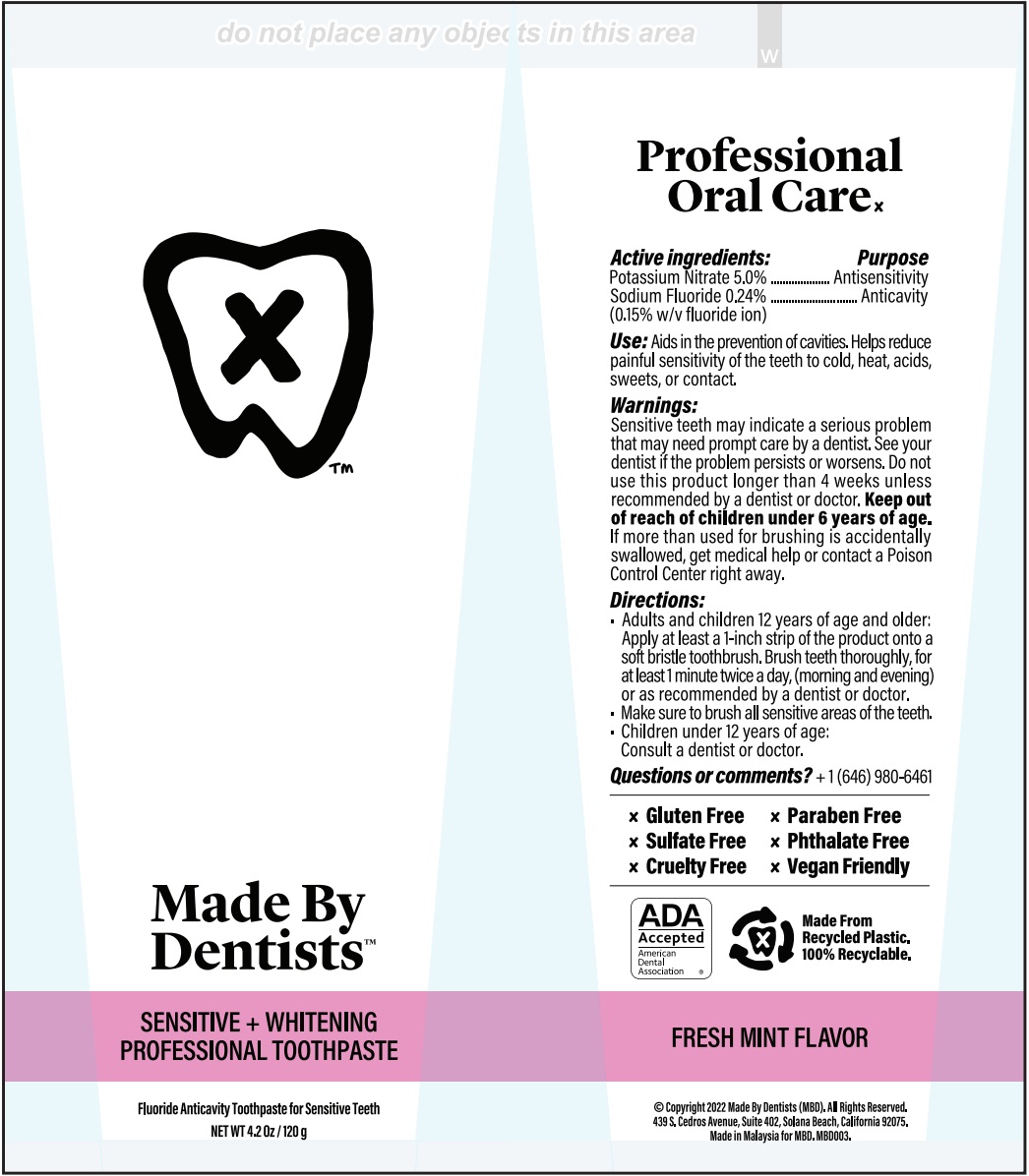 DRUG LABEL: Made by Dentists Sensitive and Whitening Professional
NDC: 62776-004 | Form: PASTE
Manufacturer: Fulijaya Manufacturing Sdn. Bhd
Category: otc | Type: HUMAN OTC DRUG LABEL
Date: 20250623

ACTIVE INGREDIENTS: POTASSIUM NITRATE 50 mg/1 g; SODIUM FLUORIDE 1.5 mg/1 g
INACTIVE INGREDIENTS: WATER; SORBITOL; HYDRATED SILICA; XYLITOL; COCAMIDOPROPYL BETAINE; CARBOXYMETHYLCELLULOSE SODIUM, UNSPECIFIED; SODIUM TRIPOLYPHOSPHATE ANHYDROUS; TITANIUM DIOXIDE; SACCHARIN SODIUM; POTASSIUM SORBATE; HYDROGEN PEROXIDE; SODIUM BICARBONATE

Made by Dentists Sensitive + Whitening Professional Toothpaste

Active ingredient:

Potassium Nitrate 5.0%

Sodium Fluoride 0.24% (0.15% w/v fluoride ion)

Purpose

Antisensitivity

Anticavity

Use:

Aids in the prevention of cavities. Helps reduce painful sensitivity of the teeth to cold, heat, acids, sweets, or contact.

Warnings:

Sensitive teeth may indicate a serious problem that may need prompt care by a dentist. See your dentist if the problem persists or worsens. Do not use this product longer than 4 weeks unless recommended by a dentist or doctor.

Keep out of reach of children under 6 years of age.

If more than used for brushing is accidentlly swallowed, get medical help or contact a Poison Control Center right away.

Directions:

- Adults and children 12 years of age and older: Apply at least a 1-inch strip of the product onto a soft bristle toothbrush. Brush teeth thoroughly, for at least 1 minute twice a day, (morning and evening) or as recommended by a dentist or doctor.
- Make sure to brush all sensitive areas of the teeth.
- Children under 12 years of age: Consult a dentist or doctor.

Inactive ingredients:

Water (Aqua), Sorbitol, Hydrated Silica, Xylitol, Flavor, Cocamidopropyl Betaine, Cellulose Gum, Pentasodium Triphosphate, Titanium Dioxide, Sodium Saccharin, Potassium Sorbate, Hydrogen Peroxide, Sodium Bicarbonate

Questions or comments?

+ 1 (646) 980-6461